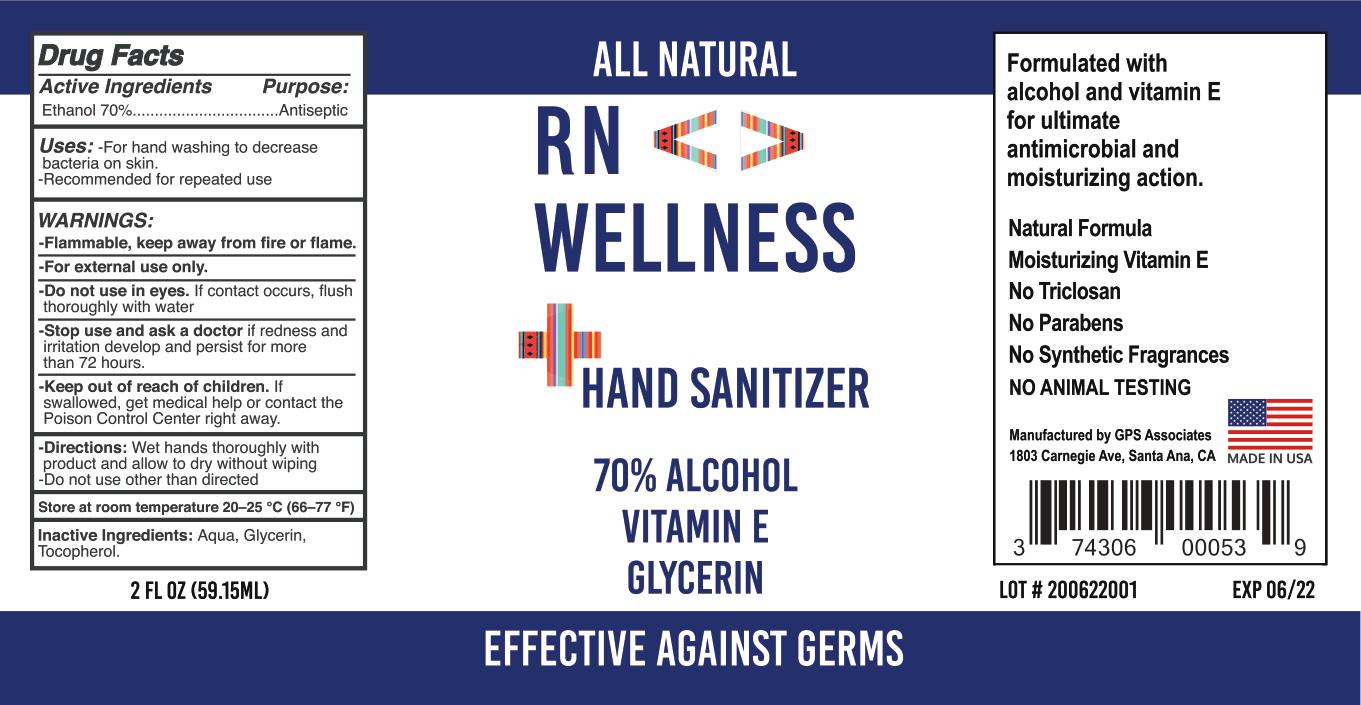 DRUG LABEL: RN Wellness Sanitizer
NDC: 79556-123 | Form: LIQUID
Manufacturer: RN Wellness
Category: otc | Type: HUMAN OTC DRUG LABEL
Date: 20200710

ACTIVE INGREDIENTS: ALCOHOL 70 mL/100 mL
INACTIVE INGREDIENTS: THYME OIL; WATER; ORANGE OIL; GLYCERIN; .ALPHA.-TOCOPHEROL, DL-

Active Ingredients

Ethanol 70%

Purpose:

Antiseptic

Uses:

-For hand washing to decrease bacteria on skin.

-Recommended for repeated use

WARNINGS:

-Flammable, keep away from fire or flame.

WHEN USING

-For external use only.

-Do not use in eyes. If contact occurs, flush thoroughly with water

-Stop use and ask a doctor if redness and irritation develop and persist for more than 72 hours.

-Keep out of reach of children. If swallowed, get medical help or contact the Poison Control Center right away.

-Directions:

Wet hands thoroughly with product and allow to dry without wiping

-Do not use other than directed

STORAGE AND HANDLING

Store at room temperature 20-25 °C (66-77 °F)

Inactive Ingredients: Aqua, Glycerin, Tocopherol.